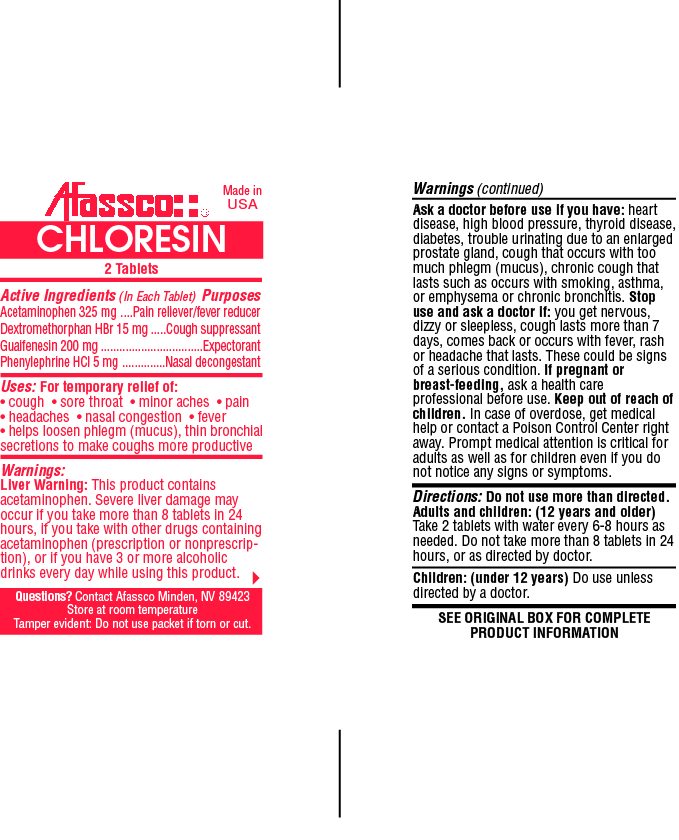 DRUG LABEL: Chloresin
NDC: 51532-0107 | Form: TABLET
Manufacturer: Affasco Inc.
Category: otc | Type: HUMAN OTC DRUG LABEL
Date: 20190921

ACTIVE INGREDIENTS: ACETAMINOPHEN 325 1/1 1; DEXTROMETHORPHAN HYDROBROMIDE 15 1/1 1; GUAIFENESIN 200 1/1 1; PHENYLEPHRINE HYDROCHLORIDE 5 1/1 1
INACTIVE INGREDIENTS: STARCH, CORN; CELLULOSE, MICROCRYSTALLINE; POVIDONE; SODIUM STARCH GLYCOLATE TYPE A CORN; STEARIC ACID; MALTODEXTRIN; SILICON DIOXIDE

Active Ingredients (In Each Tablet)

Acetaminophen 325 mg, Dextromethorphan HBr 15 mg, Guaifenesin 200 mg, Phenylephrine HCl 5 mg

PURPOSE

Pain reliever/fever reducer, Cough suppressant, Expectorant, Nasal decongestant

INDICATIONS AND USAGE

Uses: For temporary relief of:

• cough • sore throat • minor aches • pain

• headaches • nasal congestion • fever

• helps loosen phlegm (mucus), thin bronchial secretions to make coughs more productive

Warnings:

Liver Warning:

This product contains acetaminophen. Severe liver damage may occur if you take more than 8 tablets in 24 hours, if you take with other drugs containing acetaminophen (prescription or nonprescription), or if you have 3 or more alcoholic drinks every day while using this product.

Ask a doctor before use if you have: heart disease, high blood pressure, thyroid disease, diabetes, trouble urinating due to an enlarged prostate gland, cough that occurs with too much phlegm (mucus), chronic cough that lasts such as occurs with smoking, asthma, or emphysema or chronic bronchitis.

Stop use and ask a doctor if: you get nervous, dizzy or sleepless, cough lasts more than 7 days, comes back or occurs with fever, rash or headache that lasts. These could be signsof a serious condition.

PREGNANCY OR BREAST FEEDING

If pregnant or breast-feeding, ask a health professional before use.

KEEP OUT OF REACH OF CHILDREN.

OVERDOSAGE

In case of overdose, get medical help or contact a Poison Control Center right away. Prompt medical attention is critical for adults as well as for children even if you do not notice any signs or symptoms.

DOSAGE AND ADMINISTRATION

Directions: Do not use more than directed.

Adults and children: (12 years and older) Take 2 tablets with water every 6-8 hours as needed. Do not take more than 8 tablets in 24 hours, or as directed by doctor.

Children: (under 12 years) Do use unless directed by a doctor.

INACTIVE INGREDIENT

SEE ORIGINAL BOX FOR COMPLETE PRODUCT INFORMATION

PACKAGE LABEL

res